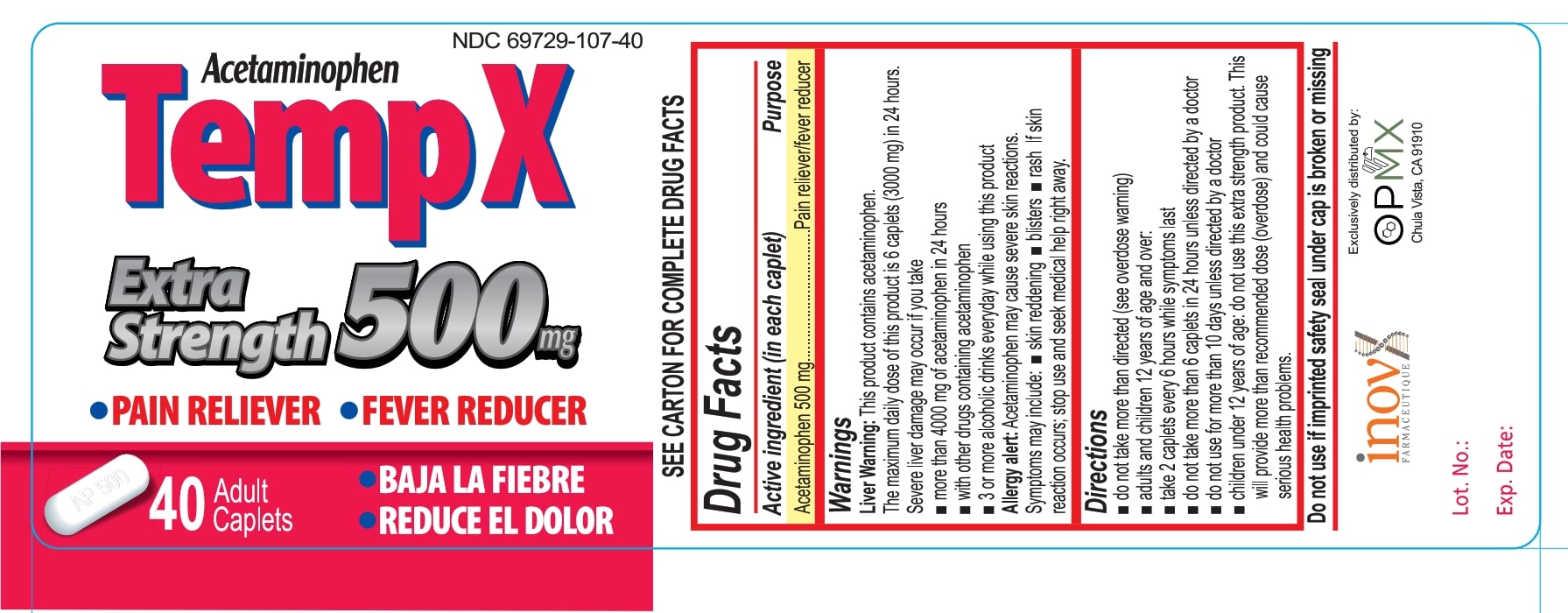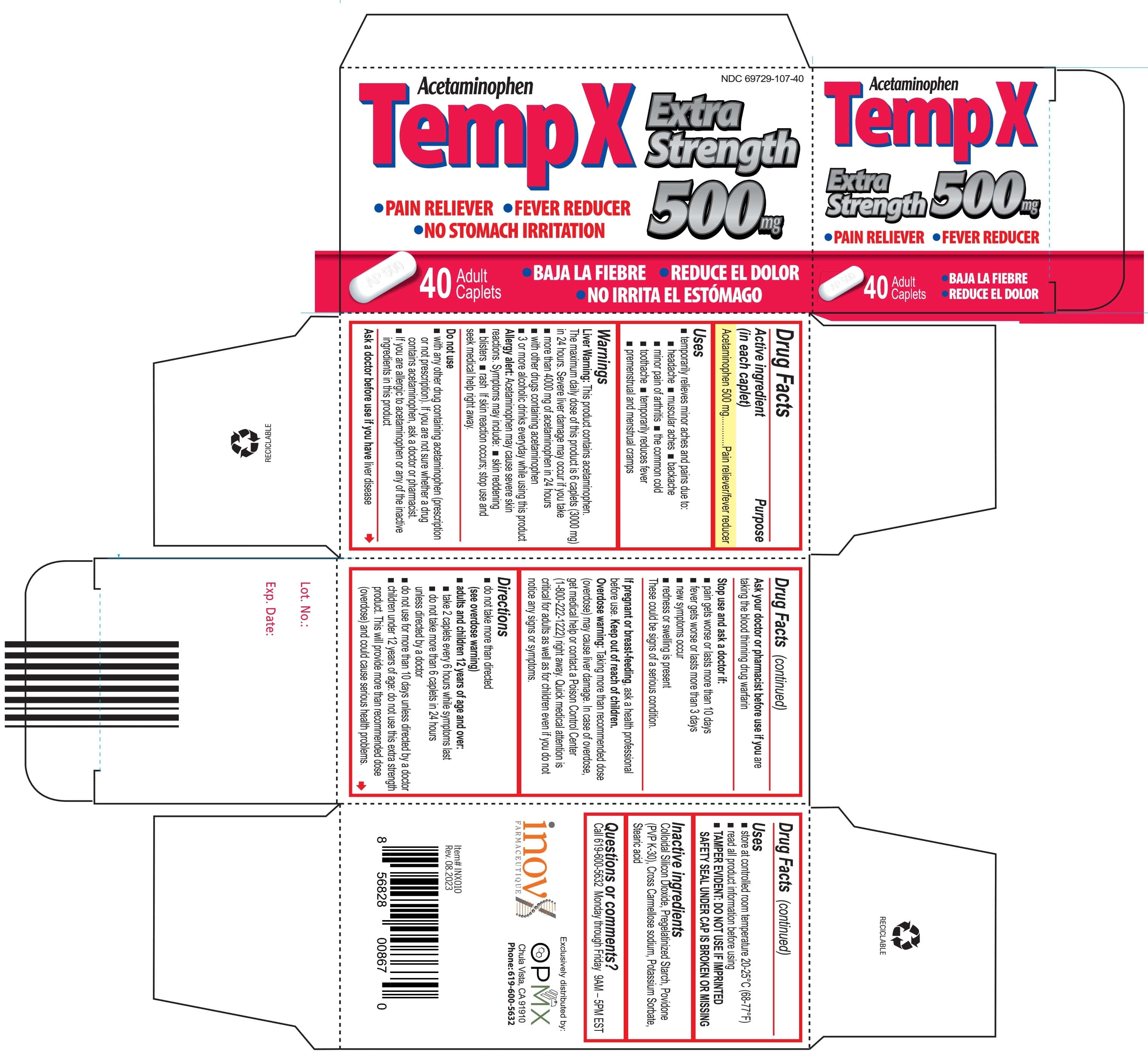 DRUG LABEL: Extra Strenghth Acetaminophen
NDC: 69729-107 | Form: TABLET
Manufacturer: OPMX LLC
Category: otc | Type: HUMAN OTC DRUG LABEL
Date: 20250319

ACTIVE INGREDIENTS: ACETAMINOPHEN 500 mg/1 1
INACTIVE INGREDIENTS: STARCH, PREGELATINIZED CORN; POVIDONE K30; SILICON DIOXIDE; STEARIC ACID; POTASSIUM SORBATE; CROSCARMELLOSE SODIUM

Temp X Caplets

Active Ingredient

(in each tablet)

Acetaminophen 500mg

Purpose

Pain reliever/fever reducer

Uses

Temporary relieves minor aches and pains due to:

- headache
- muscular aches
- backache
- minor pain of arthritis
- the common cold
- toothache
- temporarily reduces fever
- premenstrual and menstrual cramps

Warnings

Liver warning:This product contains acetaminophen. The maximum daily dose of this product is 6 caplets (3000 mg) in 24 hours. Severe liver damage may occur if you take

- more than 4,000 mg of acetaminophen in 24 hours
- with other drugs containing acetaminophen
- 3 or more alcoholic drinks every day while using this product

Allergy alert:Acetaminophen may cause severe skin reactions. Symptoms may include:

- skin reddening
- blisters
- rash

If a skin reaction occurs; stop use and seek medical help right away.

Do not use

- with any other drug containing acetaminophen (prescription or nonprescription). If you are not sure whether a drug contains acetaminophen, ask a doctor or pharmacist.
- if you have ever had an allergic reaction to this product or any of its ingredients

Ask a doctor before use if you have

- liver disease

Ask a doctor or pharmacist before use if you are

- taking the blood thinning drug warfarin

Stop use and ask a doctor if

- pain gets worse or lasts more than 10 days
- fever gets worse or lasts more than 3 days
- new symptoms occur
- redness or swelling is present

These could be signs of a serious condition.

If pregnant or breast-feeding

ask a health professional before use

Keep out of reach of children.

Overdose warning:Taking more than the reccomended dose (overdose) may cause liver damage. In case of overdose. get medical help or contact a Poison Control Center (1-800-222-1222) right away. Quick medical attention is critical for adults as well as for children even if you do not notice any signs or symptoms.

Directions

- do not use more than directed (see overdose warning)

Adults and children 12 years of age and older:

- Take 2 caplets every 6 hours while symptoms last.
- Do not take more than 6 caplets in 24 hours, unless directed by a doctor
- Do not use more than 10 days unless directed by a doctor.

Children under 12 years of age: Do not use this extra strength product. This will provide more than the recommended dose (overdose) and could cause serious health problems.

Other Information

- store at controlled room temperature 20-25°C (68-77°F).
- read all product information before using.
- TAMPER EVIDENT: DO NOT USE IF IMPRINTED SAFETY SEAL UNDER CAP IS BROKEN OR MISSING.

Inactive Ingredients

Colloidal silicon dioxide, pregelatinized starch, povidone (pvp k-30), croscarmellose sodium, potassium sorbate, stearic acid

Questions or Comments

Call 619-600-5632 Monday through Friday 9AM-5PM EST